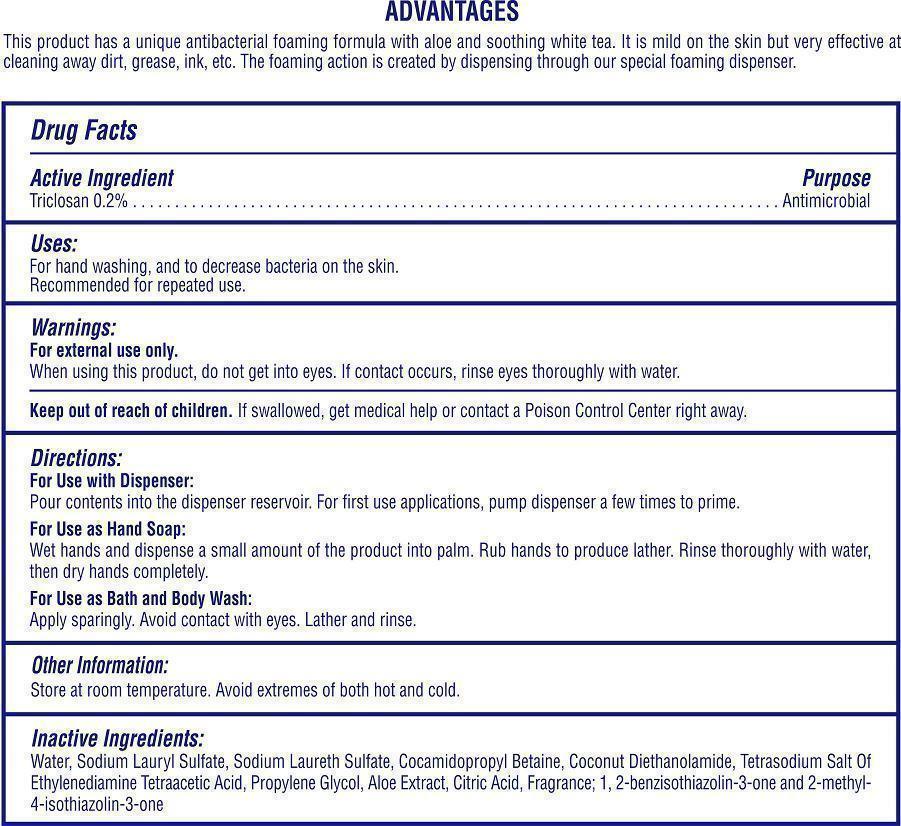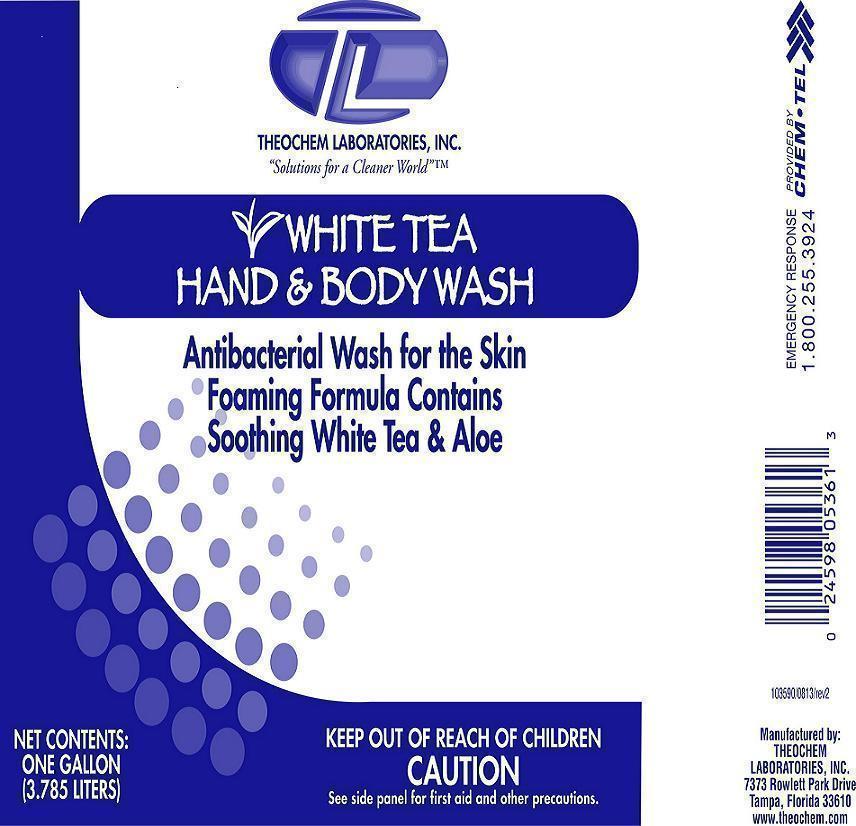 DRUG LABEL: Theochem White Tea Hand and Body Wash
NDC: 68878-130 | Form: SOAP
Manufacturer: Theochem Laboratories Inc
Category: otc | Type: HUMAN OTC DRUG LABEL
Date: 20131008

ACTIVE INGREDIENTS: TRICLOSAN 2 g/1 L
INACTIVE INGREDIENTS: WATER

White Tea Hand and Body Wash

Active Ingredient

Triclosan 0.2%

Purpose

Antimicrobial

Uses:

For hand washing, and to decrease bacteria on the skin.

Recommended for repeated use.

Warnings:

For external use only.

When using this product, do not get into eyes. If contact occurs, rinse eyes thoroughly with water.

Keep out of reach of children.

If swallowed, get medical help or contact a Poison Control Center right away.

Directions:

For Use with Dispenser:

Pour contents into the dispenser reservoir. For first use applications, pump dispenser a few times to prime.

For Use as Hand Soap:

Wet hands and dispense a small amount of the product in palm. Rub hands to produce lather. Rinse thoroughly with water, then dry hands completely.

For Use as Bath and Body Wash:

Apply sparingly. Avoid contact with eyes. Lather and rinse.

Other Information:

Store at room temperature. Avoid extremes of both hot and cold.

Inactive Ingredients:

Water, Sodium Lauryl Sulfate, Sodium Laureth Sulfate, Cocamidopropyl Betaine, Coconut Diethanolamide, Tetrasodium Salt of Ethylenediamine Tetraacetic Acid, Propylene Glycol, Aloe Extract, Citric Acid, Fragrance; 1,2-benzisothiazolin-3-one and 2-methyl-4-isothiazolin-3-one.